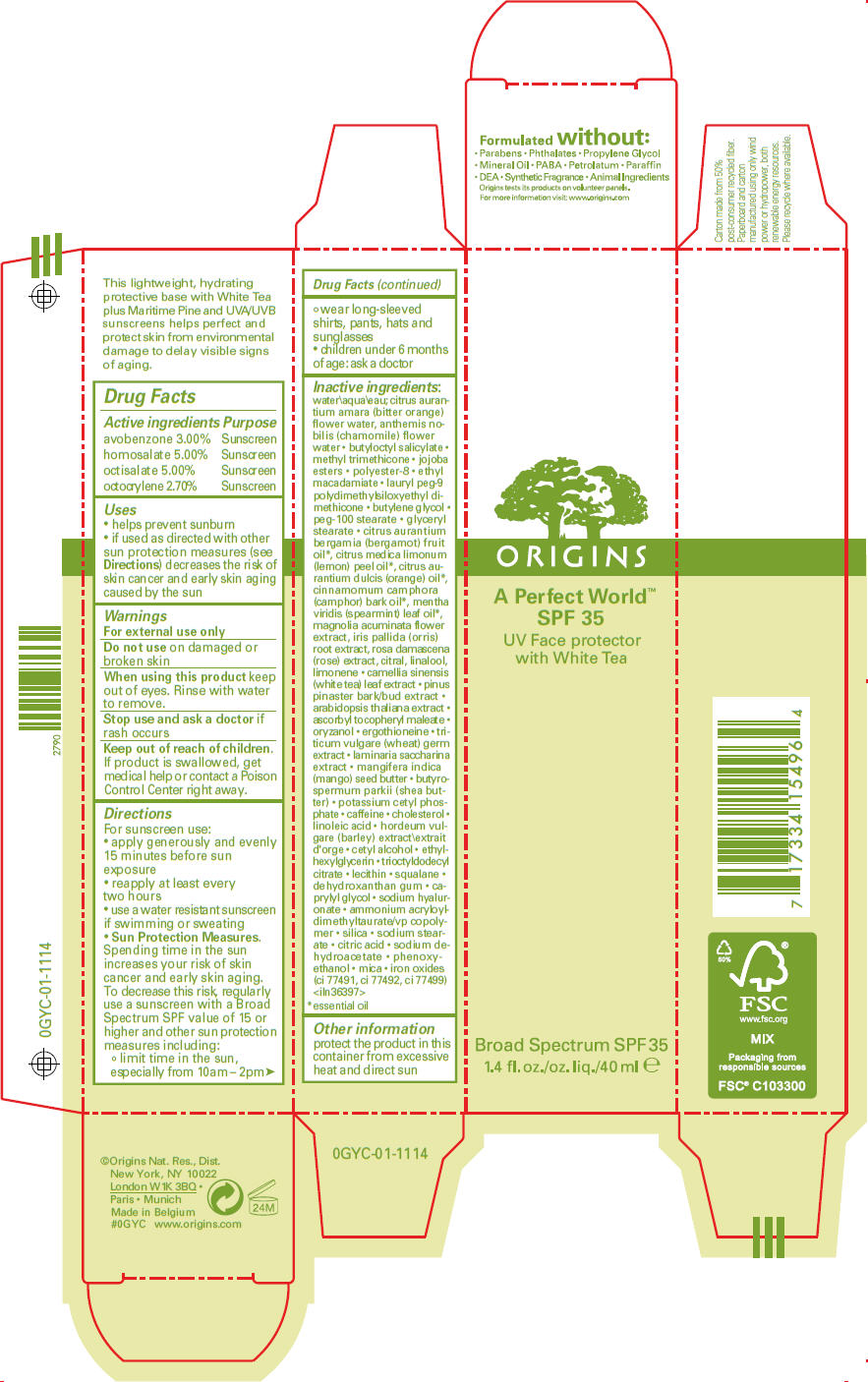 DRUG LABEL: A PERFECT WORLD 
NDC: 59427-706 | Form: LOTION
Manufacturer: ORIGINS NATURAL RESOURCES INC
Category: otc | Type: HUMAN OTC DRUG LABEL
Date: 20120405

ACTIVE INGREDIENTS: HOMOSALATE 5 mL/100 mL; OCTISALATE 5 mL/100 mL; AVOBENZONE 3 mL/100 mL; OCTOCRYLENE 2.7 mL/100 mL
INACTIVE INGREDIENTS: water; citrus aurantium flower oil; chamaemelum nobile flower oil; butyloctyl salicylate; methyl trimethicone; ethyl macadamiate; butylene glycol; peg-100 stearate; glyceryl monostearate; bergamot oil; lemon oil; orange oil; camphor oil; spearmint oil; magnolia acuminata flower; iris pallida root; rosa damascena flower; citral; linalool, (+/-)-; maritime pine; gamma oryzanol; ergothioneine; wheat germ; saccharina latissima thallus; mangifera indica seed butter; shea butter; potassium cetyl phosphate; caffeine; cholesterol; linoleic acid; cetyl alcohol; ethylhexylglycerin; squalane; caprylyl glycol; hyaluronate sodium; ammonium acryloyldimethyltaurate/vp copolymer; silicon dioxide; sodium stearate; citric acid monohydrate; sodium dehydroacetate; phenoxyethanol; mica; ferric oxide red; ferric oxide yellow; ferrosoferric oxide

A Perfect World™
SPF 35 UV BROAD SPECTRUM FACE PROTECTOR

Drug Facts

ACTIVE INGREDIENT

Active ingredients | Purpose
avobenzone 3.00% | Sunscreen
homosalate 5.00% | Sunscreen
octisalate 5.00% | Sunscreen
octocrylene 2.70% | Sunscreen

Uses

- helps prevent sunburn
- if used as directed with other sun protection measures (see Directions) decreases the risk of skin cancer and early skin aging caused by the sun

Warnings

For external use only

Do not use on damaged or broken skin

When using this product keep out of eyes. Rinse with water to remove.

Stop use and ask a doctor if rash occurs

Keep out of reach of children. If product is swallowed, get medical help or contact a Poison Control Center right away.

Directions

For sunscreen use:

- apply generously and evenly 15 minutes before sun exposure
- reapply at least every two hours
- use a water resistant sunscreen if swimming or sweating
- Sun Protection Measures. Spending time in the sun increases your risk of skin cancer and early skin aging. To decrease this risk, regularly use a sunscreen with a Broad Spectrum SPF value of 15 or higher and other sun protection measures including:
  - limit time in the sun, especially from 10am – 2pm
  - wear long-sleeved shirts, pants, hats and sunglasses
- children under 6 months of age: ask a doctor

Inactive ingredients

water\aqua\eau; citrus aurantium amara (bitter orange) flower water, anthemis nobilis (chamomile) flower water • butyloctyl salicylate • methyl trimethicone • jojoba esters • polyester-8 • ethyl macadamiate • lauryl peg-9 polydimethylsiloxyethyl dimethicone • butylene glycol • peg-100 stearate • glyceryl stearate • citrus aurantium bergamia (bergamot) fruit oil [essential oil] , citrus medica limonum (lemon) peel oil, citrus aurantium dulcis (orange) oil, cinnamomum camphora (camphor) bark oil, mentha viridis (spearmint) leaf oil, magnolia acuminata flower extract, iris pallida (orris) root extract, rosa damascena (rose) extract, citral, linalool, limonene • camellia sinensis (white tea) leaf extract • pinus pinaster bark/bud extract • arabidopsis thaliana extract • ascorbyl tocopheryl maleate • oryzanol • ergothioneine • triticum vulgare (wheat) germ extract • laminaria saccharina extract • mangifera indica (mango) seed butter • butyrospermum parkii (shea butter) • potassium cetyl phosphate • caffeine • cholesterol • linoleic acid • hordeum vulgare (barley) extract\extrait d'orge • cetyl alcohol • ethylhexylglycerin • trioctyldodecyl citrate • lecithin • squalane • dehydroxanthan gum • caprylyl glycol • sodium hyaluronate • ammonium acryloyldimethyltaurate/vp copolymer • silica • sodium stearate • citric acid • sodium dehydroacetate • phenoxyethanol • mica • iron oxides (ci 77491, ci 77492, ci 77499) <iln36397>

Other information

protect the product in this container from excessive heat and direct sun

Dist.
New York, NY 10022

PRINCIPAL DISPLAY PANEL - 40 ml Tube Carton

ORIGINS

A Perfect World™
SPF 35
UV Face protector
with White Tea

Broad Spectrum SPF 35
1.4 fl. oz./oz. liq./40 ml e